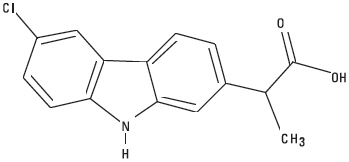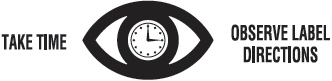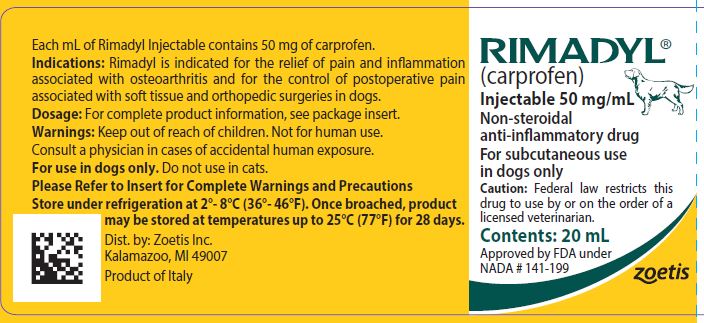 DRUG LABEL: Rimadyl
NDC: 54771-8507 | Form: INJECTION, SOLUTION
Manufacturer: Zoetis Inc.
Category: animal | Type: PRESCRIPTION ANIMAL DRUG LABEL
Date: 20220323

ACTIVE INGREDIENTS: Carprofen 50 mg/1 mL
INACTIVE INGREDIENTS: arginine 30 mg/1 mL; glycocholic acid; lecithin, soybean; benzyl alcohol; sodium hydroxide; hydrochloric acid

RIMADYL®

RIMADYL®
(carprofen)
Sterile Injectable Solution
50 mg/mL

Non-steroidal anti-inflammatory drug

For subcutaneous use in dogs only

CAUTION

Federal law restricts this drug to use by or on the order of a licensed veterinarian.

DESCRIPTION

Rimadyl Injectable is a sterile solution containing carprofen, a non-steroidal anti-inflammatory drug (NSAID) of the propionic acid class that includes ibuprofen, naproxen, and ketoprofen. Carprofen is the non-proprietary designation for a substituted carbazole, 6-chloro-α-methyl-9H-carbazole-2-acetic acid. The empirical formula is C15H12CINO2 and molecular weight 273.72.

The chemical structure of carprofen is:

Each mL of Rimadyl Injectable contains 50.0 mg carprofen, 30.0 mg arginine, 88.5 mg glycocholic acid, 169.0 mg lecithin, 10.0 mg benzyl alcohol, 6.17 mg sodium hydroxide, with additional sodium hydroxide and hydrochloric acid as needed to adjust pH, and water for injection.

CLINICAL PHARMACOLOGY

Carprofen is a non-narcotic, non-steroidal anti-inflammatory agent with characteristic analgesic and antipyretic activity approximately equipotent to indomethacin in animal models.^1

The mechanism of action of carprofen, like that of other NSAIDs, is believed to be associated with the inhibition of cyclooxygenase activity. Two unique cyclooxygenases have been described in mammals.^2 The constitutive cyclooxygenase, COX-1, synthesizes prostaglandins necessary for normal gastrointestinal and renal function. The inducible cyclooxygenase, COX-2, generates prostaglandins involved in inflammation. Inhibition of COX-1 is thought to be associated with gastrointestinal and renal toxicity while inhibition of COX-2 provides anti-inflammatory activity. The specificity of a particular NSAID for COX-2 versus COX-1 may vary from species to species.^3 In an in vitro study using canine cell cultures, carprofen demonstrated selective inhibition of COX-2 versus COX-1.^4 Clinical relevance of these data has not been shown. Carprofen has also been shown to inhibit the release of several prostaglandins in two inflammatory cell systems: rat polymorphonuclear leukocytes (PMN) and human rheumatoid synovial cells, indicating inhibition of acute (PMN system) and chronic (synovial cell system) inflammatory reactions.^1

Several studies have demonstrated that carprofen has modulatory effects on both humoral and cellular immune responses.^5–9 Data also indicate that carprofen inhibits the production of osteoclast-activating factor (OAF), PGE1, and PGE2 by its inhibitory effects on prostaglandin biosynthesis.^1

Based upon comparison with data obtained from intravenous administration, carprofen is rapidly and nearly completely absorbed (more than 90% bioavailable) when administered orally.^10 Peak blood plasma concentrations are achieved in 1–3 hours after oral administration of 1, 5, and 25 mg/kg to dogs.The mean terminal half-life of carprofen is approximately 8 hours (range 4.5–9.8 hours) after single oral doses varying from 1–35 mg/kg of body weight. After a 100 mg single intravenous bolus dose, the mean elimination half-life was approximately 11.7 hours in the dog. Rimadyl is more than 99% bound to plasma protein and exhibits a very small volume of distribution. Comparison of a single 25 mg dose in Beagle dogs after subcutaneous and oral administration demonstrated that the dorsoscapular subcutaneous administration results in a slower rate of drug input (as reflected by mean peak observed concentrations) but comparable total drug absorption within a 12 hour dosing interval (as reflected by area under the curve from hours zero to 12 postdose). Carprofen is eliminated in the dog primarily by biotransformation in the liver followed by rapid excretion of the resulting metabolites (the ester glucuronide of carprofen and the ether glucuronides of 2 phenolic metabolites, 7-hydroxy carprofen and 8-hydroxy carprofen) in the feces (70–80%) and urine (10–20%). Some enterohepatic circulation of the drug is observed.

INDICATIONS

Rimadyl is indicated for the relief of pain and inflammation associated with osteoarthritis and for the control of postoperative pain associated with soft tissue and orthopedic surgeries in dogs.

CONTRAINDICATIONS

Rimadyl should not be used in dogs exhibiting previous hypersensitivity to carprofen.

WARNINGS

Keep out of reach of children. Not for human use. Consult a physician in cases of accidental human exposure. For use in dogs only. Do not use in cats.

All dogs should undergo a thorough history and physical examination before initiation of NSAID therapy. Appropriate laboratory tests to establish hematological and serum biochemical baseline data prior to, and periodically during, administration of any NSAID should be considered. Owners should be advised to observe for signs of potential drug toxicity (see Adverse Reactions, Animal Safety and Post-Approval Experience).

PRECAUTIONS

As a class, cyclooxygenase inhibitory NSAIDs may be associated with gastrointestinal, renal and hepatic toxicity. Effects may result from decreased prostaglandin production and inhibition of the enzyme cyclooxygenase which is responsible for the formation of prostaglandins from arachidonic acid.^11–14 When NSAIDs inhibit prostaglandins that cause inflammation they may also inhibit those prostaglandins which maintain normal homeostatic function. These anti-prostaglandin effects may result in clinically significant disease in patients with underlying or pre-existing disease more often than in healthy patients.^12,14 NSAID therapy could unmask occult disease which has previously been undiagnosed due to the absence of apparent clinical signs. Patients with underlying renal disease for example, may experience exacerbation or decompensation of their renal disease while on NSAID therapy.^11–14 The use of parenteral fluids during surgery should be considered to reduce the potential risk of renal complications when using NSAIDs perioperatively.

Carprofen is an NSAID, and as with others in that class, adverse reactions may occur with its use. The most frequently reported effects have been gastrointestinal signs. Events involving suspected renal, hematologic, neurologic, dermatologic, and hepatic effects have also been reported. Patients at greatest risk for renal toxicity are those that are dehydrated, on concomitant diuretic therapy, or those with renal, cardiovascular, and/or hepatic dysfunction. Concurrent administration of potentially nephrotoxic drugs should be approached cautiously, with appropriate monitoring. Concomitant use of Rimadyl with other anti-inflammatory drugs, such as other NSAIDs or corticosteroids, should be avoided because of the potential increase of adverse reactions, including gastrointestinal ulcerations and/or perforations. Sensitivity to drug-associated adverse reactions varies with the individual patient. Dogs that have experienced adverse reactions from one NSAID may experience adverse reactions from another NSAID. Rimadyl treatment was not associated with renal toxicity or gastrointestinal ulceration in well-controlled safety studies of up to ten times the dose in healthy dogs. As with any parenterally injected product, good hygienic procedures should be used when administering Rimadyl Injectable. It is suggested to use different sites for additional injections.

Rimadyl is not recommended for use in dogs with bleeding disorders (e.g., Von Willebrand's disease), as safety has not been established in dogs with these disorders. The safe use of Rimadyl in animals less than 6 weeks of age, pregnant dogs, dogs used for breeding purposes, or in lactating bitches has not been established. Safety has not been established for IV or IM administration. Studies to determine the activity of Rimadyl when administered concomitantly with other protein-bound or similarly metabolized drugs have not been conducted. Drug compatibility should be monitored closely in patients requiring additional therapy. Such drugs commonly used include cardiac, anticonvulsant and behavioral medications. It has been suggested that treatment with carprofen may reduce the level of inhalant anesthetics needed.15 If additional pain medication is warranted after administration of the total daily dose of Rimadyl, alternative analgesia should be considered. The use of another NSAID is not recommended. Consider appropriate washout times when switching from one NSAID to another or when switching from corticosteroid use to NSAID use.

INFORMATION FOR DOG OWNERS:

Rimadyl, like other drugs of its class, is not free from adverse reactions.Owners should be advised of the potential for adverse reactions and be informed of the clinical signs associated with drug intolerance. Adverse reactions may include decreased appetite, vomiting, diarrhea, dark or tarry stools, increased water consumption, increased urination, pale gums due to anemia, yellowing of gums, skin or white of the eye due to jaundice, lethargy, incoordination, seizure, or behavioral changes. Serious adverse reactions associated with this drug class can occur without warning and in rare situations result in death (see Adverse Reactions). Owners should be advised to discontinue Rimadyl therapy and contact their veterinarian immediately if signs of intolerance are observed. The vast majority of patients with drug related adverse reactions have recovered when the signs are recognized, the drug is withdrawn, and veterinary care, if appropriate, is initiated. Owners should be advised of the importance of periodic follow up for all dogs during administration of any NSAID.

ADVERSE REACTIONS

During investigational studies for the caplet formulation, no clinically significant adverse reactions were reported. Some clinical signs were observed during field studies (n=297) which were similar for carprofen- and placebo-treated dogs. Incidences of the following were observed in both groups: vomiting (4%), diarrhea (4%), changes in appetite (3%), lethargy (1.4%), behavioral changes (1%), and constipation (0.3%). The product vehicle served as control.There were no serious adverse events reported during clinical field studies with once daily oral administration of 2 mg/lb. The following categories of abnormal health observations were reported. The product vehicle served as control.

Percentage of Dogs with Abnormal Health Observations Reported in Clinical Field Study (2 mg/lb once daily)
Observation | Rimadyl (n=129) | Placebo (n=132)
Inappetence | 1.6 | 1.5
Vomiting | 3.1 | 3.8
Diarrhea/Soft stool | 3.1 | 4.5
Behavior change | 0.8 | 0.8
Dermatitis | 0.8 | 0.8
PU/PD | 0.8 | —
SAP increase | 7.8 | 8.3
ALT increase | 5.4 | 4.5
AST increase | 2.3 | 0.8
BUN increase | 3.1 | 1.5
Bilirubinuria | 16.3 | 12.1
Ketonuria | 14.7 | 9.1

Clinical pathology parameters listed represent reports of increases from pre-treatment values; the use of clinical judgement is necessary to determine clinical relevance (refers also to table below).

There were no serious adverse events reported during clinical field studies for the injectable formulation. The following categories of abnormal health observations were reported. Saline served as placebo control.

Percentage of Dogs with Abnormal Health Observations Reported in Clinical Field Studies with the Injectable
Observation [A single dog may have experienced more than one occurrence of an event.] | Rimadyl (n=168) | Placebo (n=163)
Vomiting | 10.1 | 9.2
Diarrhea/soft stool | 2.4 | 3.7
Dermatitis | 0.6 | 1.2
Dysrhythmia | 0.6 | 0.6
Swelling | 0 | 1.2
Dehiscence | 1.2 | 0
WBC increase | 13.7 | 6.7

* A single dog may have experienced more than one occurrence of an event.

Post-Approval Experience

Although not all adverse reactions are reported, the following adverse reactions are based on voluntary post-approval adverse drug experience reporting. The categories of adverse reactions are listed by body system.

Gastrointestinal: Vomiting, diarrhea, constipation, inappetence, melena, hematemesis, gastrointestinal ulceration, gastrointestinal bleeding, pancreatitis.

Hepatic: Inappetence, vomiting, jaundice, acute hepatic toxicity, hepatic enzyme elevation, abnormal liver function test(s), hyperbilirubinemia, bilirubinuria, hypoalbuminemia. Approximately one-fourth of hepatic reports were in Labrador Retrievers.

Neurologic: Ataxia, paresis, paralysis, seizures, vestibular signs, disorientation.

Urinary: Hematuria, polyuria, polydipsia, urinary incontinence, urinary tract infection, azotemia, acute renal failure, tubular abnormalities including acute tubular necrosis, renal tubular acidosis, glucosuria.

Behavioral: Sedation, lethargy, hyperactivity, restlessness, aggressiveness.

Hematologic: Immune-mediated hemolytic anemia, immune-mediated thrombocytopenia, blood loss anemia, epistaxis.

Dermatologic: Pruritus, increased shedding, alopecia, pyotraumatic moist dermatitis (hot spots), necrotizing panniculitis/vasculitis, ventral ecchymosis.

In rare situations, injection site reactions including necrosis, abscess and seroma formation, and granulomas have been reported with the injectable formulation.

Immunologic or hypersensitivity: Facial swelling, hives, erythema.

In rare situations, death has been associated with some of the adverse reactions listed above.

To report a suspected adverse reaction call 1-888-963-8471.

DOSAGE AND ADMINISTRATION

Carefully consider the potential benefits and risks of Rimadyl and other treatment options before deciding to use Rimadyl. Use the lowest effective dose for the shortest duration consistent with individual response. The recommended dosage for subcutaneous administration to dogs is 2 mg/lb (4.4 mg/kg) of body weight daily. The total daily dose may be administered as either 2 mg/lb of body weight once daily or divided and administered as 1 mg/lb (2.2 mg/kg) twice daily. For control of postoperative pain, administer approximately 2 hours before the procedure.

EFFECTIVENESS

Confirmation of the effectiveness of Rimadyl for the relief of pain and inflammation associated with osteoarthritis, and for the control of postoperative pain associated with soft tissue and orthopedic surgeries was demonstrated in 7 placebo-controlled, masked studies examining the anti-inflammatory and analgesic effectiveness of Rimadyl caplets and injectable in various breeds of dogs.

Separate placebo-controlled, masked, multicenter field studies confirmed the anti-inflammatory and analgesic effectiveness of Rimadyl caplets when dosed at 2 mg/lb once daily or when divided and administered at 1 mg/lb twice daily. In these two field studies, dogs diagnosed with osteoarthritis showed statistically significant overall improvement based on lameness evaluations by the veterinarian and owner observations when administered Rimadyl at labeled doses.

Based upon the blood level comparison between subcutaneous and oral administration, Rimadyl effectiveness for osteoarthritis after dorsoscapular subcutaneous and oral administration should be similar, although there may be a slight delay in the onset of relief after subcutaneous injection.

Separate placebo-controlled, masked, multicenter field studies confirmed the effectiveness of Rimadyl injectable for the control of postoperative pain when dosed at 2 mg/lb once daily in various breeds of dogs. In these studies, dogs presented for ovariohysterectomy, cruciate repair and aural surgeries were administered Rimadyl preoperatively and for a maximum of 3 days (soft tissue) or 4 days (orthopedic) postoperatively. In general, dogs administered Rimadyl showed statistically significant improvement in pain scores compared to controls.

ANIMAL SAFETY

Laboratory studies in unanesthetized dogs and clinical field studies have demonstrated that Rimadyl is well tolerated in dogs after oral and subcutaneous administration.

In target animal safety studies, Rimadyl was administered orally to healthy Beagle dogs at 1, 3, and 5 mg/lb twice daily (1, 3 and 5 times the recommended total daily dose) for 42 consecutive days with no significant adverse reactions. Serum albumin for a single female dog receiving 5 mg/lb twice daily decreased to 2.1 g/dL after 2 weeks of treatment, returned to the pre-treatment value (2.6 g/dL) after 4 weeks of treatment, and was 2.3 g/dL at the final 6-week evaluation. Over the 6-week treatment period, black or bloody stools were observed in 1 dog (1 incident) treated with 1 mg/lb twice daily and in 1 dog (2 incidents) treated with 3 mg/lb twice daily. Redness of the colonic mucosa was observed in 1 male that received 3 mg/lb twice daily.

Two of 8 dogs receiving 10 mg/lb orally twice daily (10 times the recommended total daily dose) for 14 days exhibited hypoalbuminemia. The mean albumin level in the dogs receiving this dose was lower (2.38 g/dL) than each of 2 placebo control groups (2.88 and 2.93 g/dL, respectively). Three incidents of black or bloody stool were observed in 1 dog. Five of 8 dogs exhibited reddened areas of duodenal mucosa on gross pathologic examination. Histologic examination of these areas revealed no evidence of ulceration, but did show minimal congestion of the lamina propria in 2 of the 5 dogs.

In separate safety studies lasting 13 and 52 weeks, respectively, dogs were administered orally up to 11.4 mg/lb/day (5.7 times the recommended total daily dose of 2 mg/lb) of carprofen. In both studies, the drug was well tolerated clinically by all of the animals. No gross or histologic changes were seen in any of the treated animals. In both studies, dogs receiving the highest doses had average increases in serum L-alanine aminotransferase (ALT) of approximately 20 IU.

In the 52 week study, minor dermatologic changes occurred in dogs in each of the treatment groups but not in the control dogs. The changes were described as slight redness or rash and were diagnosed as non-specific dermatitis. The possibility exists that these mild lesions were treatment related, but no dose relationship was observed.

Clinical field studies were conducted with 549 dogs of different breeds at the recommended oral doses for 14 days (297 dogs were included in a study evaluating 1 mg/lb twice daily and 252 dogs were included in a separate study evaluating 2 mg/lb once daily). In both studies the drug was clinically well tolerated and the incidence of clinical adverse reactions for Rimadyl-treated animals was no higher than placebo-treated animals (placebo contained inactive ingredients found in Rimadyl). For animals receiving 1 mg/lb twice daily, the mean post-treatment serum ALT values were 11 IU greater and 9 IU less than pre-treatment values for dogs receiving Rimadyl and placebo, respectively. Differences were not statistically significant. For animals receiving 2 mg/lb once daily, the mean post-treatment serum ALT values were 4.5 IU greater and 0.9 IU less than pre-treatment values for dogs receiving Rimadyl and placebo, respectively. In the latter study, 3 Rimadyl-treated dogs developed a 3-fold or greater increase in (ALT) and/or (AST) during the course of therapy. One placebo-treated dog had a greater than 2-fold increase in ALT. None of these animals showed clinical signs associated with the laboratory value changes. Changes in clinical laboratory values (hematology and clinical chemistry) were not considered clinically significant. The 1 mg/lb twice daily course of therapy was repeated as needed at 2-week intervals in 244 dogs, some for as long as 5 years.

Clinical field studies were conducted on 331 dogs undergoing orthopedic or soft tissue surgery. Dogs were administered 2 mg/lb of Rimadyl subcutaneously two hours prior to surgery and once daily thereafter, as needed, for 2 days (soft tissue surgery) or 3 days (orthopedic surgery). Rimadyl was well tolerated when used in conjunction with a variety of anesthetic-related drugs. The type and severity of abnormal health observations in Rimadyl- and placebo-treated animals were approximately equal and few in number (see Adverse Reactions). The most frequent abnormal health observation was vomiting and was observed at approximately the same frequency in Rimadyl- and placebo-treated animals. Changes in clinicopathologic indices of hematopoietic, renal, hepatic, and clotting function were not clinically significant. The mean post-treatment serum ALT values were 8.4 IU and 7.0 IU less than pre-treatment values for dogs receiving Rimadyl and placebo, respectively. The mean post-treatment AST values were 1.5 IU and 0.7 IU greater for dogs receiving Rimadyl and placebo, respectively.

Swelling and warmth were associated with the injection site after subcutaneous administration of Rimadyl injectable. These findings were not clinically significant. Long term use of the injectable has not been studied.

STORAGE

Store under refrigeration 2°-8°C (36°-46°F). Once broached, product may be stored at temperatures up to 25°C (77°F) for 28 days.

HOW SUPPLIED

Rimadyl Injectable is supplied in 20-mL, amber, glass, sterile, multi-dose vials.

REFERENCES

1. Baruth H, et al: In Anti-Inflammatory and Anti-Rheumatic Drugs, Vol. II, Newer Anti-Inflammatory Drugs, Rainsford KD, ed. CRC Press, Boca Raton, pp. 33–47, 1986.
2. Vane JR, Botting RM: Mechanism of action of anti-inflammatory drugs. Scand J Rheumatol 25:102, pp. 9–21.
3. Grossman CJ, Wiseman J, Lucas FS, et al: Inhibition of constitutive and inducible cyclooxygenase activity in human platelets and mononuclear cells by NSAIDs and COX-2 inhibitors. Inflammation Research 44:253–257, 1995.
4. Ricketts AP, Lundy KM, Seibel SB: Evaluation of selective inhibition of canine cyclooxgenase 1 and 2 by carprofen and other nonsteroidal anti-inflammatory drugs. Am J Vet Res 59:11, pp. 1441–1446, November 1998.
5. Ceuppens JL, et al: Non-steroidal anti-inflammatory agents inhibit the synthesis of IgM rheumatoid factor in vitro. Lancet 1:528, 1982.
6. Ceuppens JL, et al: Endogenous prostaglandin E2 enhances polyclonal immunoglobulin production by ionically inhibiting T suppressor cell activity. Cell Immunol 70:41, 1982.
7. Schleimer RP, et al: The effects of prostaglandin synthesis inhibition on the immune response. Immunopharmacology 3:205, 1981.
8. Leung KH, et al: Modulation of the development of cell mediated immunity: possible roles of the products of cyclooxgenase and lipoxygenase pathways of arachidonic acid metabolism. Int J Immunopharmacology 4:195, 1982.
9. Veit BC: Immunoregulatory activity of cultured-induced suppressor macrophages. Cell Immunol 72:14, 1982.
10. Schmitt M, et al: Biopharmaceutical evaluation of carprofen following single intravenous, oral, and rectal doses in dogs. Biopharm Drug Dispos 11(7):585–94, 1990.
11. Kore AM: Toxicology of nonsteroidal anti-inflammatory drugs. Veterinary Clinics of North America, Small Animal Practice 20, March 1990.
12. Binns SH: Pathogenesis and pathophysiology of ischemic injury in cases of acute renal failure. Compend for Cont Ed 16:1, January 1994.
13. Boothe DM: Prostaglandins: Physiology and clinical implications. Compend for Cont Ed 6:11, November 1984.
14. Rubin SI: Nonsteroidal anti-inflammatory drugs, prostaglandins, and the kidney. JAVMA 188:9, May 1986.
15. Ko CH, Lange DN, Mandsager RE, et al: Effects of butorphanol and carprofen on the minimal alveolar concentration of isoflurane in dogs. JAVMA 217:1025–1028, 2000.

For a copy of the Safety Data Sheet (SDS) or to report adverse reactions call Zoetis at 1-888-963-8471.

Approved by FDA under NADA # 141-199

zoetis

Distributed by:
Zoetis Inc.
Kalamazoo, MI 49007

Product of Italy

October 2020
40032881

PRINCIPAL DISPLAY PANEL - 20 mL Vial Label

40032879